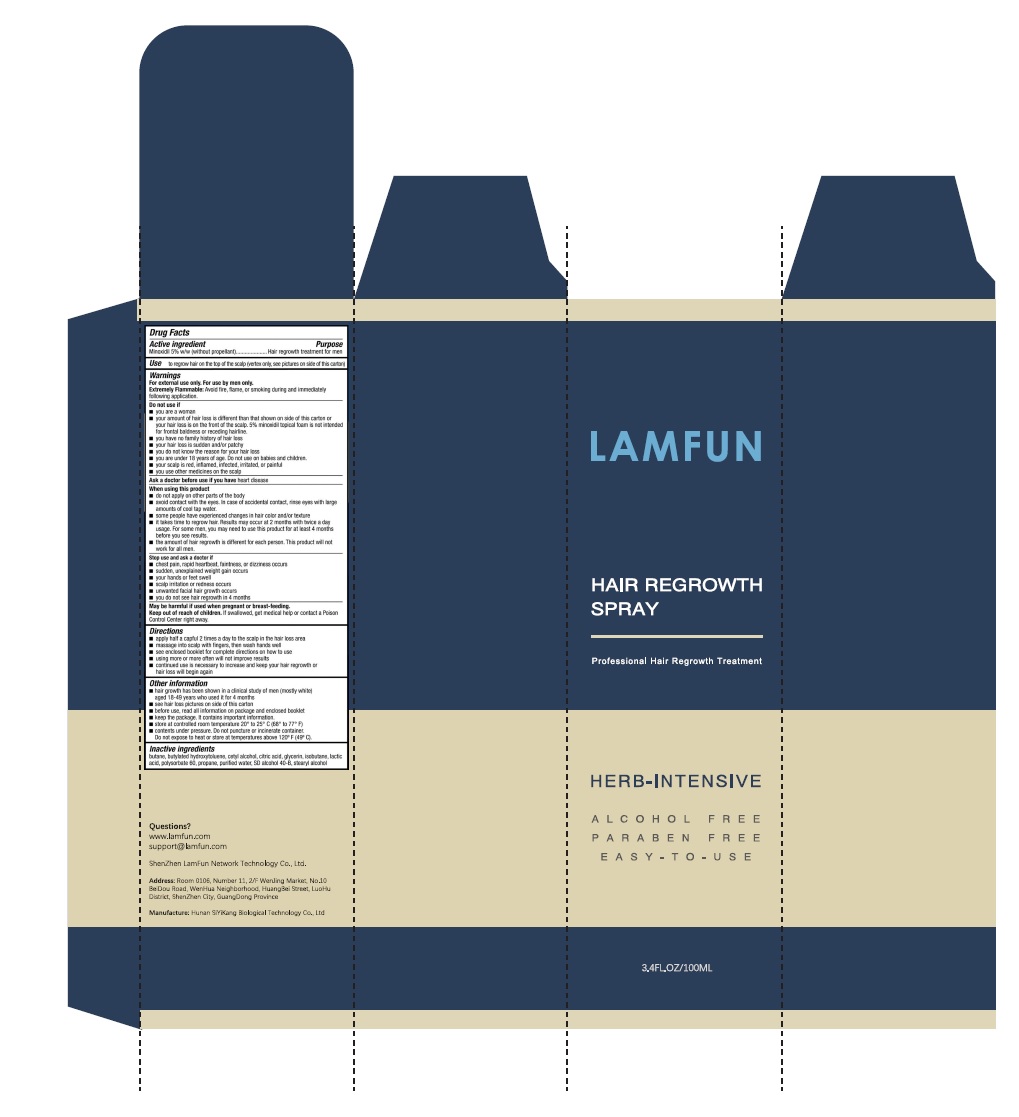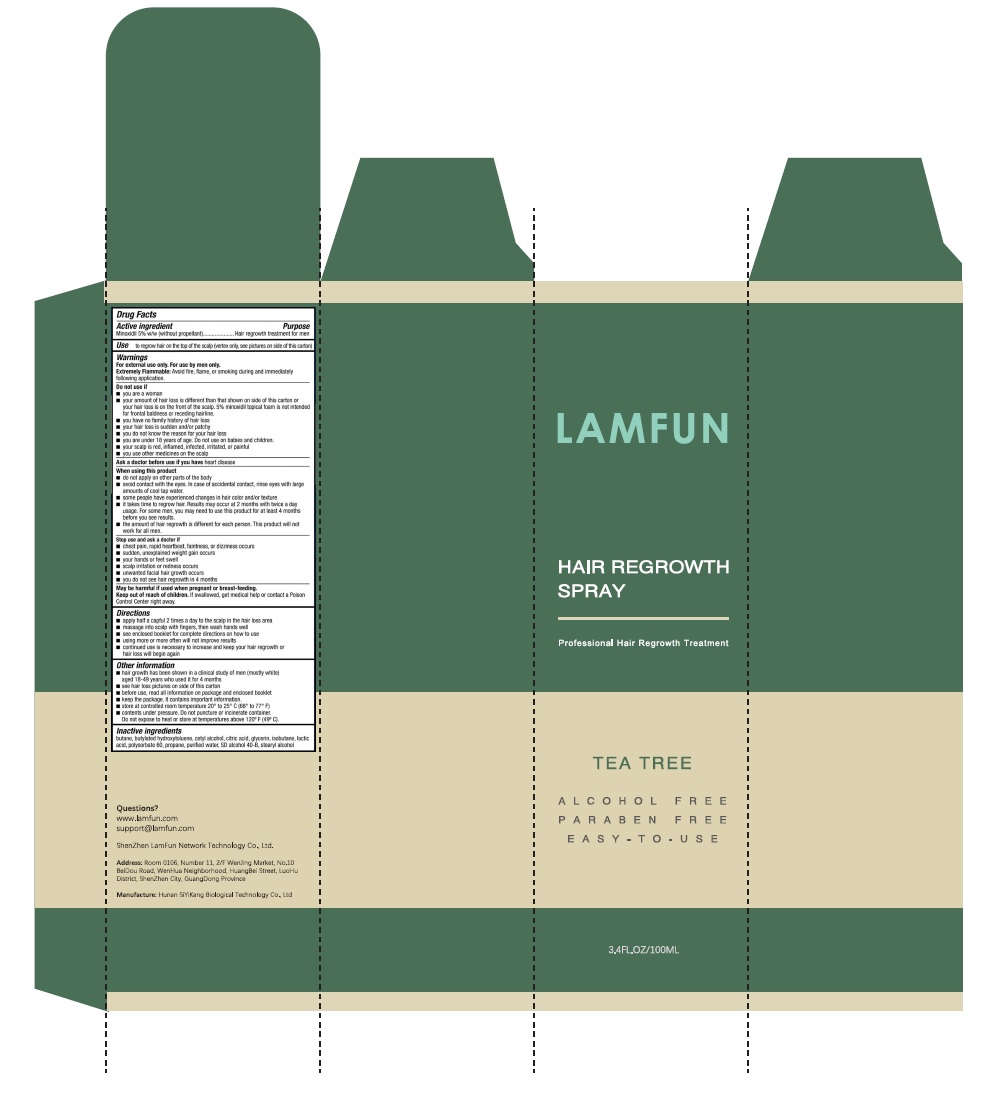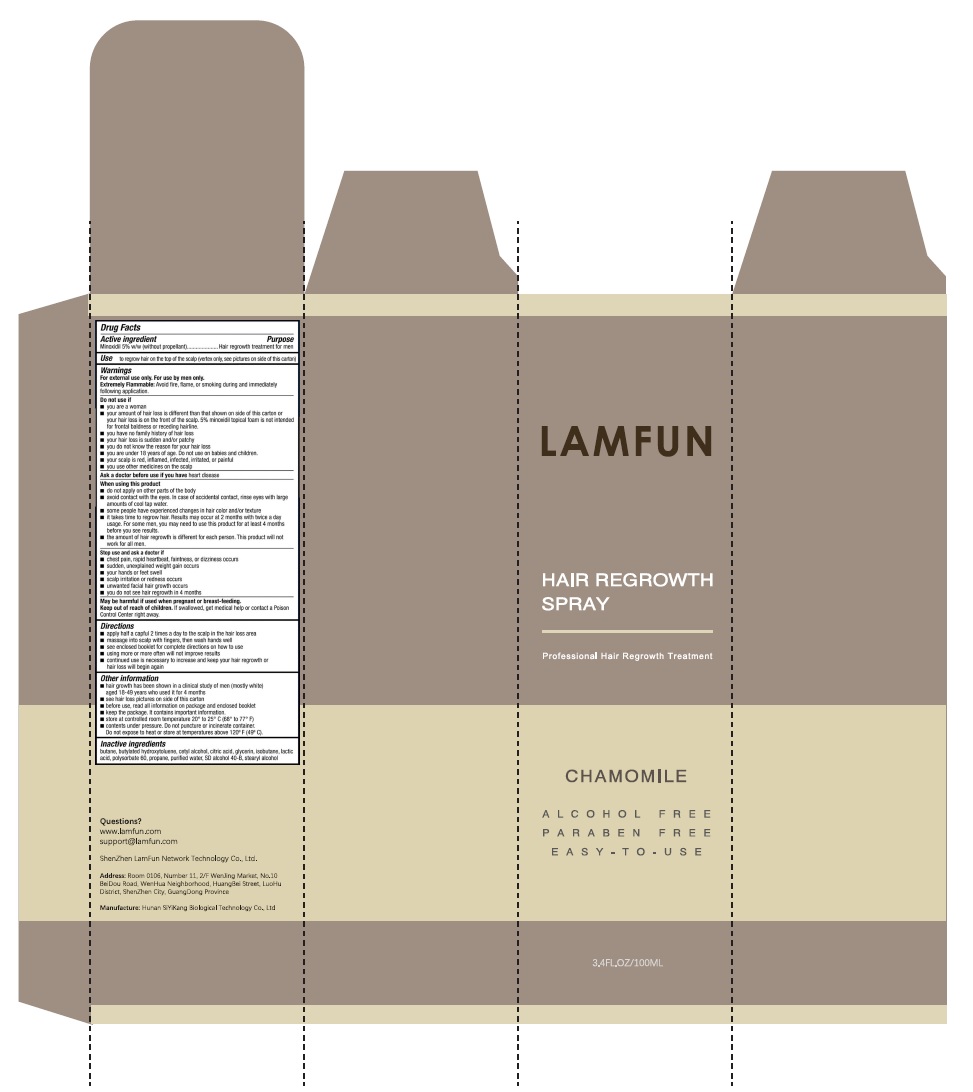 DRUG LABEL: LamFun Hair Regrowth Treatment
NDC: 74770-001 | Form: SOLUTION
Manufacturer: Shenzhen Lanfan Network Technology Co., Ltd.
Category: otc | Type: HUMAN OTC DRUG LABEL
Date: 20200406

ACTIVE INGREDIENTS: MINOXIDIL 5 g/100 mL
INACTIVE INGREDIENTS: BUTYLATED HYDROXYTOLUENE; BUTANE; CETYL ALCOHOL; GLYCERIN; CITRIC ACID MONOHYDRATE

LamFun Hair Regrowth Treatment

DOSAGE AND ADMINISTRATION

apply half a capful 2 times a day to the scalp in the hair loss area

massage into scalp with fingers, then wash hands well

see enclosed booklet for complete directions on how to use

using more or more often will not improve results

continued use is necessary to increase and keep your hair regrowth or loss will begin again

WARNINGS

For external use only. Flammable. Keep away from heat or flame

INDICATIONS AND USAGE

to regrow hair on the top of the scalp

Keep out of reach of children. If swallowed, get medical help or contact a Poison Control Center right away.

PURPOSE

to regrow hair on the top of the scalp

ACTIVE INGREDIENT

Minoxidil 5% m/v

INACTIVE INGREDIENT

butane,butylated hydroxytoluene,cetyl alcohol,citric acid，glycerin

INACTIVE INGREDIENT

butane,butylated hydroxytoluene,cetyl alcohol,citric acid，glycerin

Package Label - Principal Display Panel

100 mL 74770-001-01